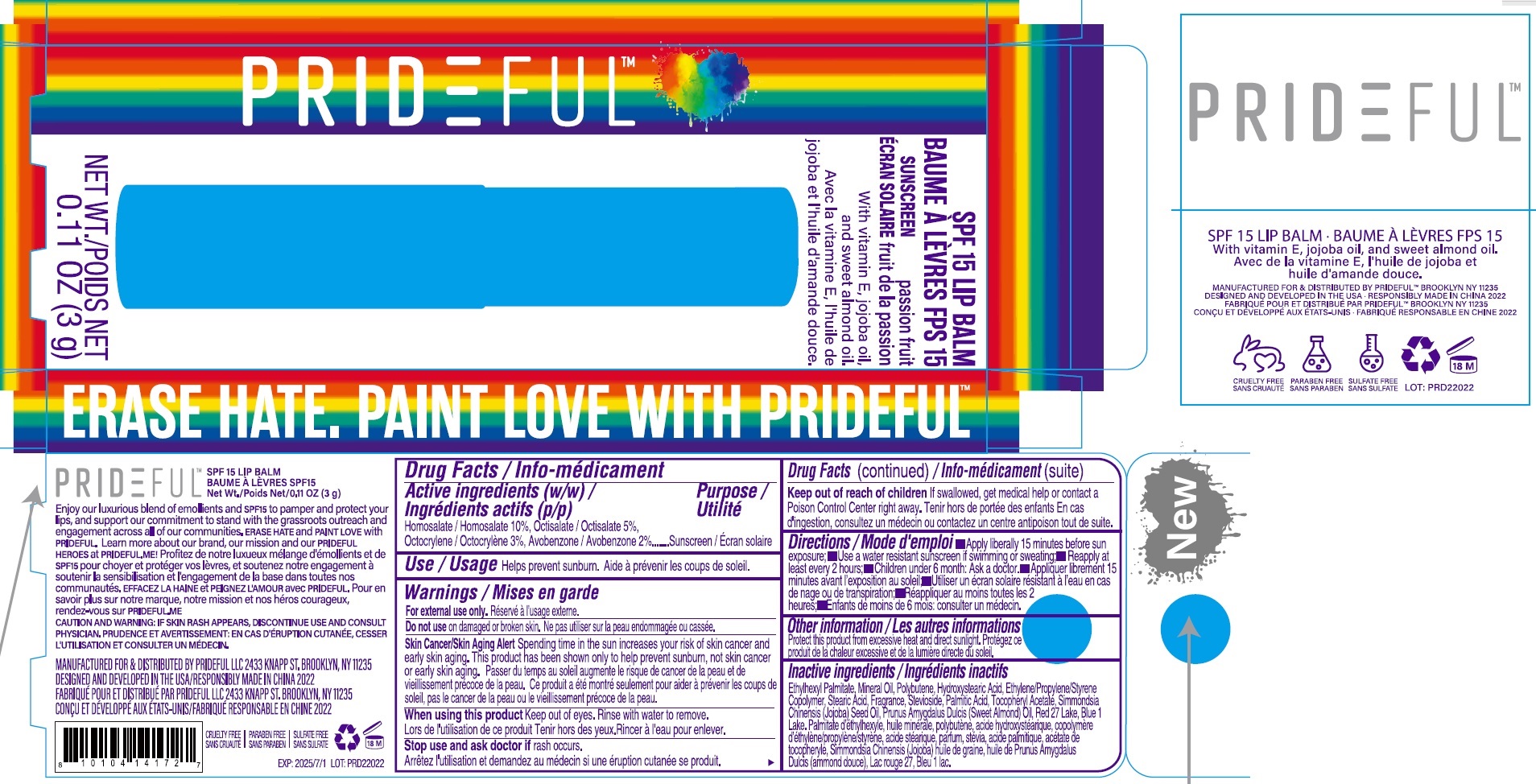 DRUG LABEL: PRIDEFUL SPF 15 LIP BALM-passion fruit
NDC: 82866-005 | Form: STICK
Manufacturer: PRIDEFUL LLC
Category: otc | Type: HUMAN OTC DRUG LABEL
Date: 20231026

ACTIVE INGREDIENTS: HOMOSALATE 100 mg/1 g; OCTISALATE 50 mg/1 g; OCTOCRYLENE 30 mg/1 g; AVOBENZONE 20 mg/1 g
INACTIVE INGREDIENTS: ETHYLHEXYL PALMITATE; MINERAL OIL; 12-HYDROXYSTEARIC ACID; ETHYLENE; PROPYLENE; STEARIC ACID; STEVIOSIDE; PALMITIC ACID; .ALPHA.-TOCOPHEROL ACETATE; JOJOBA OIL; ALMOND OIL; D&C RED NO. 27; FD&C BLUE NO. 1 ALUMINUM LAKE

PRIDEFUL SPF 15 LIP BALM-passion fruit

Active ingredients (w/w)

Homosalate 10% Octisalate 5%

Octocrylene 3% Avobenzone 2%

Purpose

Susncreen

Use

Helps prevent sunburn.

Warnings

For external use only.

Do not use

on damaged or broken skin.

Spending time in the sun increases your risk of skin cancer and early skin aging. This product has been shown only to help prevent sunrbun, not skin cancer or early skin aging. Skin Cancer/Skin Aging Alert

When using this product

Keep out of eyes. Rinse with water to remove.

Stop use and ask doctor

if rash occurs.

Keep out of reach of children

If swallowed, get medical help or contact a Poison Control Center right away.

Directions

- Apply liberally 15 minutes before sun exposure;
- Use a water resistant sunscreen if swimming or swimming or sweating
- Reapply at least every 2 hours;
- Children under 6 month: Ask a doctor.

Other information

Protect this product from excessive heat and direct sunlight.

Inactive ingredients

Ethylhexyl Palmitate, Mineral Oil, Polybutene, Hydroxystearic Acid, Ethylene/Propylene/Styrene Copolymer, Stearic Acid, Fragrance, Stevioside, Palmitic Acid, Tocopheryl Acetate, Simmondsia Chinensis (Jojoba) Seed Oil, Prunus, Amygdalus Dulcis (Sweet Almond) Oil, Red 27 Lake, Blue 1 Lake, Palmitate